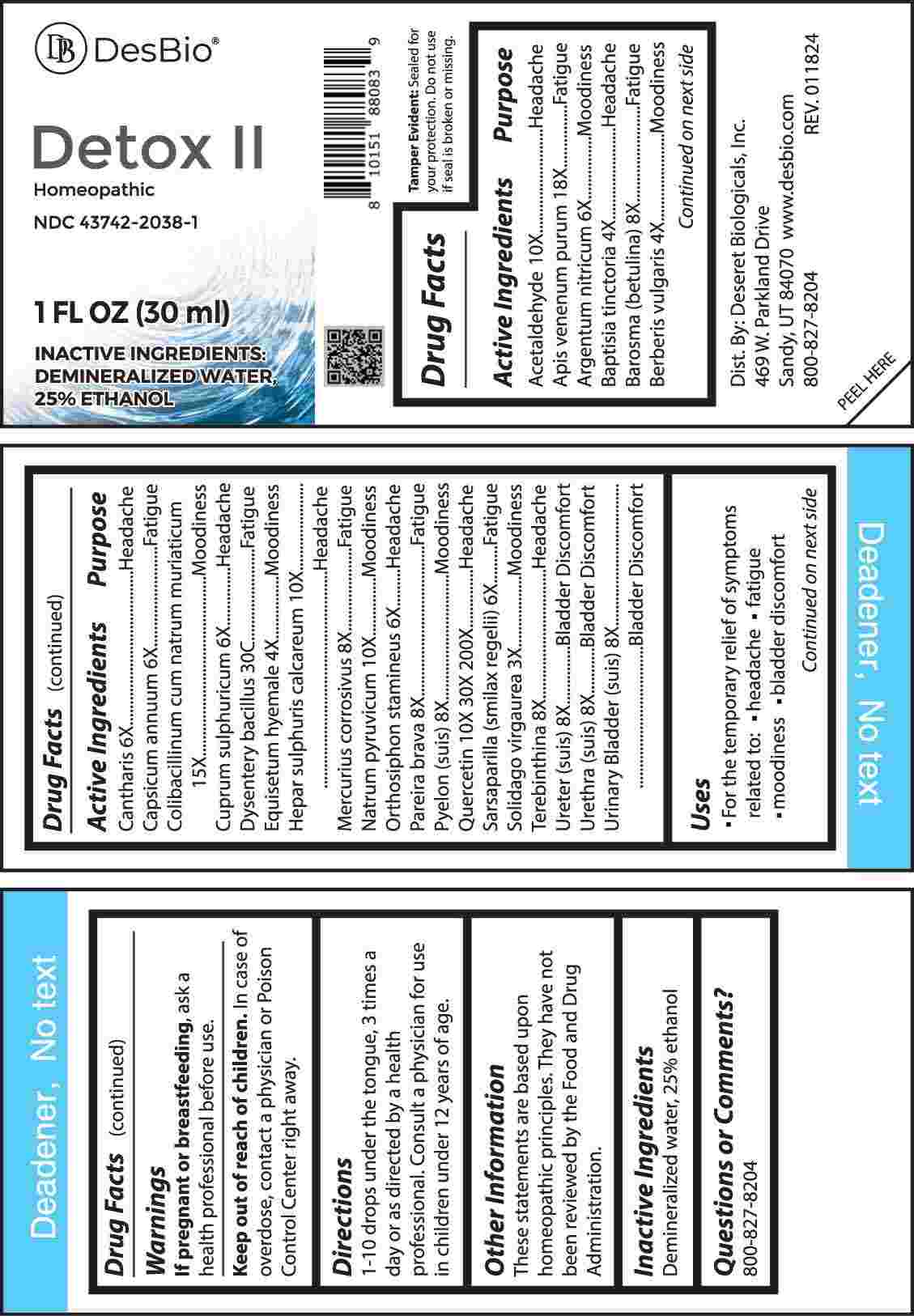 DRUG LABEL: Detox
NDC: 43742-2038 | Form: LIQUID
Manufacturer: Deseret Biologicals, Inc.
Category: homeopathic | Type: HUMAN OTC DRUG LABEL
Date: 20240502

ACTIVE INGREDIENTS: SOLIDAGO VIRGAUREA FLOWERING TOP 3 [hp_X]/1 mL; BAPTISIA TINCTORIA ROOT 4 [hp_X]/1 mL; BERBERIS VULGARIS ROOT BARK 4 [hp_X]/1 mL; EQUISETUM HYEMALE WHOLE 4 [hp_X]/1 mL; SILVER NITRATE 6 [hp_X]/1 mL; LYTTA VESICATORIA 6 [hp_X]/1 mL; CAPSICUM 6 [hp_X]/1 mL; CUPRIC SULFATE 6 [hp_X]/1 mL; ORTHOSIPHON ARISTATUS WHOLE 6 [hp_X]/1 mL; SMILAX ORNATA ROOT 6 [hp_X]/1 mL; AGATHOSMA BETULINA LEAF 8 [hp_X]/1 mL; MERCURIC CHLORIDE 8 [hp_X]/1 mL; CHONDRODENDRON TOMENTOSUM ROOT 8 [hp_X]/1 mL; SUS SCROFA RENAL PELVIS 8 [hp_X]/1 mL; TURPENTINE OIL 8 [hp_X]/1 mL; SUS SCROFA URETER 8 [hp_X]/1 mL; SUS SCROFA URETHRA 8 [hp_X]/1 mL; SUS SCROFA URINARY BLADDER 8 [hp_X]/1 mL; ACETALDEHYDE 10 [hp_X]/1 mL; CALCIUM SULFIDE 10 [hp_X]/1 mL; SODIUM PYRUVATE 10 [hp_X]/1 mL; QUERCETIN 10 [hp_X]/1 mL; ESCHERICHIA COLI 15 [hp_X]/1 mL; APIS MELLIFERA VENOM 18 [hp_X]/1 mL; SHIGELLA DYSENTERIAE 30 [hp_C]/1 mL
INACTIVE INGREDIENTS: WATER; ALCOHOL

DRUG FACTS:

ACTIVE INGREDIENTS:

Acetaldehyde 10X, Apis Venenum Purum 18X, Argentum Nitricum 6X, Baptisia Tinctoria 4X, Barosma (Betulina) 8X, Berberis Vulgaris 4X, Cantharis 6X, Capsicum Annuum 6X, Colibacillinum Cum Natrum Muriaticum 15X, Cuprum Sulphuricum 6X, Dysentery Bacillus 30C, Equisetum Hyemale 4X, Hepar Sulphuris Calcareum 10X, Mercurius Corrosivus 8X, Natrum Pyruvicum 10X, Orthosiphon Stamineus 6X, Pareira Brava 8X, Pyelon (Suis) 8X, Quercetin 10X, 30X, 200X, Sarsaparilla (Smilax Regelii) 6X, Solidago Virgaurea 3X, Terebinthina 8X, Ureter (Suis) 8X, Urethra (Suis) 8X, Urinary Bladder (Suis) 8X.

PURPOSE:

Acetaldehyde - Headache, Apis Venenum Purum - Fatigue, Argentum Nitricum - Moodiness, Baptisia Tinctoria - Headache, Barosma (Betulina) - Fatigue, Berberis Vulgaris - Moodiness, Cantharis - Headache, Capsicum Annuum - Fatigue, Colibacillinum Cum Natrum Muriaticum - Moodiness, Cuprum Sulphuricum - Headache, Dysentery Bacillus - Fatigue, Equisetum Hyemale - Moodiness, Hepar Sulphuris Calcareum - Headache, Mercurius Corrosivus - Fatigue, Natrum Pyruvicum - Moodiness, Orthosiphon Stamineus - Headache, Pareira Brava - Fatigue, Pyelon (Suis) – Moodiness, Quercetin - Headache, Sarsaparilla (Smilax Regelii) - Fatigue, Solidago Virgaurea – Moodiness, Terebinthina - Headache, Ureter (Suis) – Bladder Discomfort, Urethra (Suis) – Bladder Discomfort, Urinary Bladder (Suis) – Bladder Discomfort.

USES:

• For the temporary relief of symptoms related to:

• headache • fatigue

• moodiness • bladder discomfort

These statements are based upon homeopathic principles. They have not been reviewed by the Food and Drug Administration.

WARNINGS:

If pregnant of breast-feeding, ask a health professional before use.

Keep out of reach of children. In case of overdose, contact a physician or Poison Control Center right away.
Tamper Evident: Sealed for your protection. Do not use if seal is broken or missing.

KEEP OUT OF REACH OF CHILDREN:

In case of overdose, contact a physician or Poison Control Center right away.

DIRECTIONS:

1-10 drops under the tongue, 3 times a day or as directed by a health professional. Consult a physician for use in children under 12 years of age.

INACTIVE INGREDIENTS:

Demineralized water, 25% ethanol

QUESTIONS:

Dist. By: Deseret Biologicals, Inc.
469 W. Parkland Drive
Sandy, UT 84070

www.desbio.com

800-827-8204

PACKAGE LABEL DISPLAY:

Des Bio

Detox II

Homeopathic

NDC 43742-2038-1

1 FL OZ (30 ml)